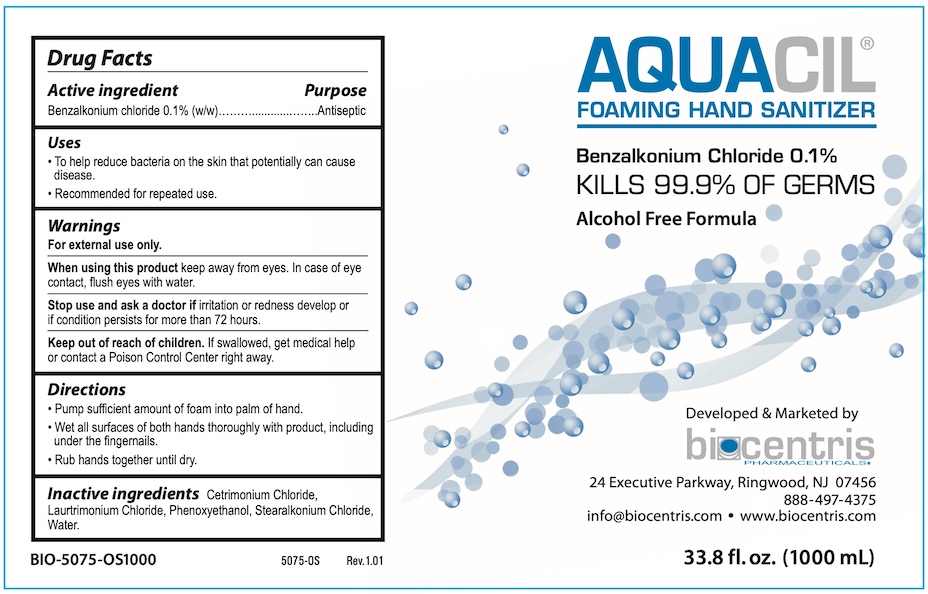 DRUG LABEL: AQUACIL
NDC: 81232-170 | Form: LIQUID
Manufacturer: Biocentris Pharmaceuticals, LLC
Category: otc | Type: HUMAN OTC DRUG LABEL
Date: 20210607

ACTIVE INGREDIENTS: BENZALKONIUM CHLORIDE 0.1 g/100 mL
INACTIVE INGREDIENTS: CETRIMONIUM CHLORIDE; LAURTRIMONIUM CHLORIDE; PHENOXYETHANOL; STEARALKONIUM CHLORIDE; WATER

Biocentris Aquacil

Drug Facts

Active ingredient

Benzalkonium chloride 0.1% (w/w)

Purpose

Antiseptic

Uses

- To help reduce bacteria on the skin that potentially can cause disease.
- Recommended for repeated use.

Warnings

For external use only.

When using this product keep away from eyes. In case of eye contact, flush eyes with water.

Stop use and ask a doctor if irritation or redness develop or if condition persists for more than 72 hours.

Keep out of reach of children. If swallowed, get medical help or contact a Poison Control Center right away.

Directions

- Pump sufficient amount of foam into palm of hand.
- Wet all surfaces of both hands thoroughly with product, including the area under the fingernails.
- Rub hands together until dry.

INACTIVE INGREDIENT

Inactive ingredients Cetrimonium Chloride, Laurtrimonium Chloride, Phenoxyethanol, Stearalkonium Chloride, Water.

Developed and Marketed by biocentris PHARMACEUTICALS

24 Executive Parkway, Ringwood, NJ 07456

888-497-4373

info@biocentris.com • www.biocentris.com

PACKAGE LABEL

AQUACIL®
FOAMING HAND SANITIZER

Benzalkonium Chloride 0.1%

KILLS 99.9% OF GERMS
Alcohol Free Formula

33.8 fl oz (1000 mL)